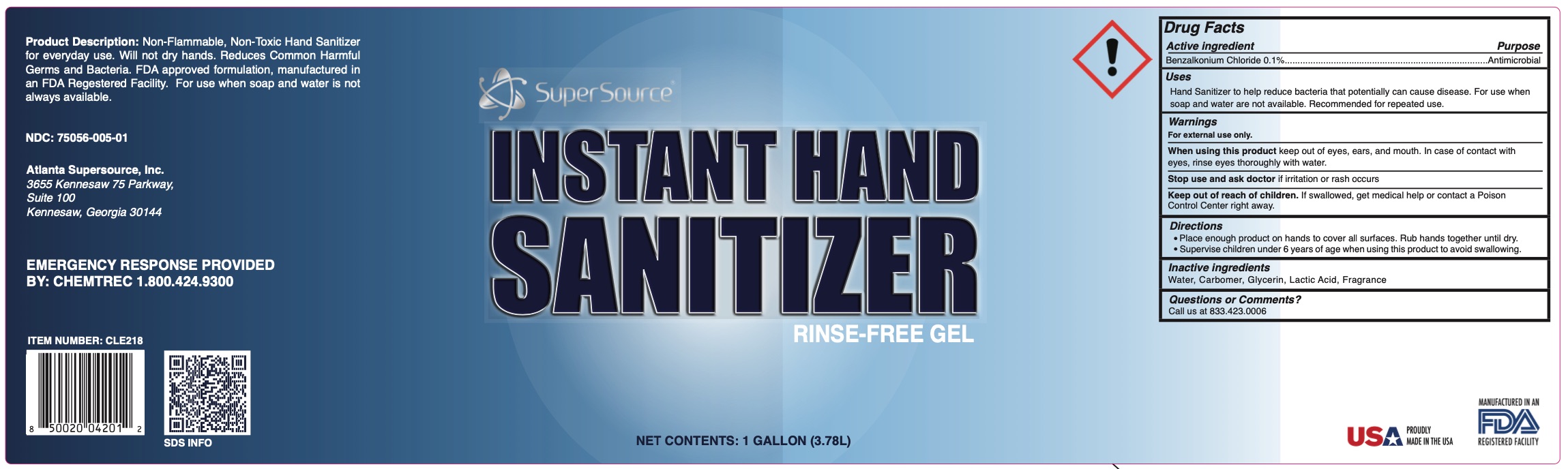 DRUG LABEL: Hand Sanitizer
NDC: 75056-005 | Form: GEL
Manufacturer: Atlanta Supersource, Inc.
Category: otc | Type: HUMAN OTC DRUG LABEL
Date: 20221222

ACTIVE INGREDIENTS: BENZALKONIUM CHLORIDE 0.1 g/100 g
INACTIVE INGREDIENTS: LACTIC ACID 7.5 g/100 g; WATER 92.072 g/100 g; CARBOMER HOMOPOLYMER, UNSPECIFIED TYPE 0.3 g/100 g; GLYCERIN 0.028 g/100 g

SS Hand Sanitizer Gel - BAC

Hand Sanitizer Gel BAC

Product Description: Non-Flammable, Non-Toxic Hand Sanitizer for everyday ese. Will not dry hands. Reduces Common Harmful Germs and Bacteria. FDA approved formulation, Manufactured in an FDA Approved Facility. For use when soap and water is not always available.

NDC: 75056-005-01

Atlanta Supersource, Inc.

3655 Kennesaw 75 Parkway

Suite 100

Kennesaw, GA 30144

EMERGENCY RESPONSE PROVIDED BY: Chemtrec 1.800.424.9300

Item Number: CLE218

Proudly made in the USA

Manufactured in a FDA registered facility

Active Ingredient(s)

Benzalkonium Chloride 0.1%

Purpose

Antimicrobial

Use

Hand Sanitizer to help reduce bacteria that potentially can cause disease. For use when soap and water are not available. Recommended for repeated use.

Warnings

For external use only.

When using this product keep out of eyes, ears, and mouth. In case of contact with eyes, rinse eyes thoroughly with water.

Stop use

Stop use and ask a doctor if irritation or rash occurs.

Keep out of reach of children. If swallowed, get medical help or contact a Poison Control Center right away.

Directions

Place enough product on hands to cover all surfaces. Rub hands together until dry.

Supervise children under 6 years of age when using this product to avoid swallowing.

Inactive Ingredients

Water, Carbomber, Glycerin, Lactic Acid, Fragrance

Questions or Comments?

Call us at 833.423.0006

Supersource Instant Hand Sanitizer Rinse-Free Gel

Net Contents: 1 Gallon (3.78L)